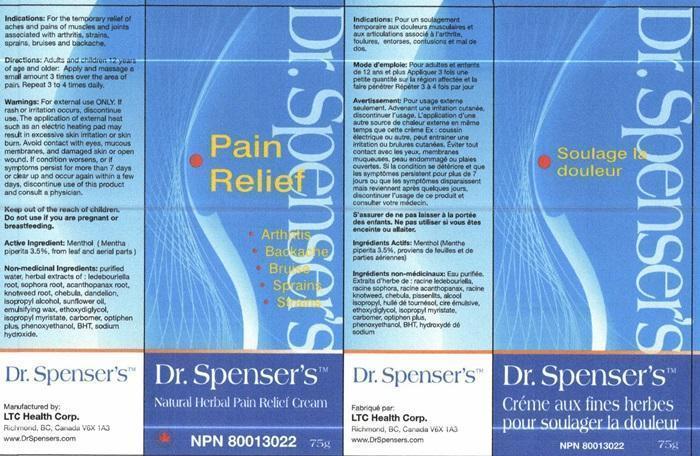 DRUG LABEL: Dr. Spensers Natural Herbal Pain Relief
NDC: 69562-022 | Form: CREAM
Manufacturer: LTC Health Corp
Category: otc | Type: HUMAN OTC DRUG LABEL
Date: 20150116

ACTIVE INGREDIENTS: MENTHOL, UNSPECIFIED FORM 2.625 g/75 g
INACTIVE INGREDIENTS: WATER; SAPOSHNIKOVIA DIVARICATA ROOT; SOPHORA FLAVESCENS ROOT; ELEUTHERO; PERSICARIA TINCTORIA LEAF; TERMINALIA CHEBULA FRUIT; TARAXACUM OFFICINALE; ISOPROPYL ALCOHOL; SUNFLOWER OIL; DIETHYLENE GLYCOL MONOETHYL ETHER; ISOPROPYL MYRISTATE; CARBOMER HOMOPOLYMER TYPE B (ALLYL SUCROSE CROSSLINKED); PHENOXYETHANOL ; BUTYLATED HYDROXYTOLUENE; SODIUM HYDROXIDE; CETOSTEARYL ALCOHOL; POLYSORBATE 60; PEG-150 STEARATE; STEARETH-20

Active Ingredient

Menthol (Mentha piperita 3.5%, from leaf and aerial parts)

Purpose

Natural Herbal Pain Relief Cream

Keep out of reach of children

Indications:

For the temporary relief of aches and pains of muscles and joints associated with arthritis, strains, sprains, bruises and backache.

Warnings:

For external use ONLY. If rash or irritation occurs, discontinue use. The application of eternal heat such as an electric heating pad may result in excessive skin irritation or skin burn. Avoid contact with eyes, mucous membranes, and damaged skin or open wound. If condition worsens, or if symptoms persist for more than 7 days or clear up and occur again within a few days, discontinue use of this product and consult a physician.

Do not use

if you are pregnant or breast feeding.

Directions:

Adults and children 12 years of age and older: Apply and massage a small amount 3 times over the area of pain. Repeat 3 to 4 times daily.

Non-medicinal Ingredients:

purified water, herbal extracts of : ledebouriella root, sophora root, acanthopanax root, knotweed root, chebula, dandelion, isopropyl alcohol, sunflower oil, emulsifying wax, ethoxydiglycol, isopropyl myristate, carbomer, optiphen plus, phenoxyethanol, BHT, sodium hydroxide

Dr. Spenser's Product Label

Dr. Spenser's™

Natural Herbal Pain Relief Cream

Pain Relief

Arthritis
Backache
Bruise
Sprains
Strains

NPN 80013022 75g

Manufactured by:
LTC Health Corp.
Richmond, BC, Canada V6X 1A3

www.DrSpensers.com